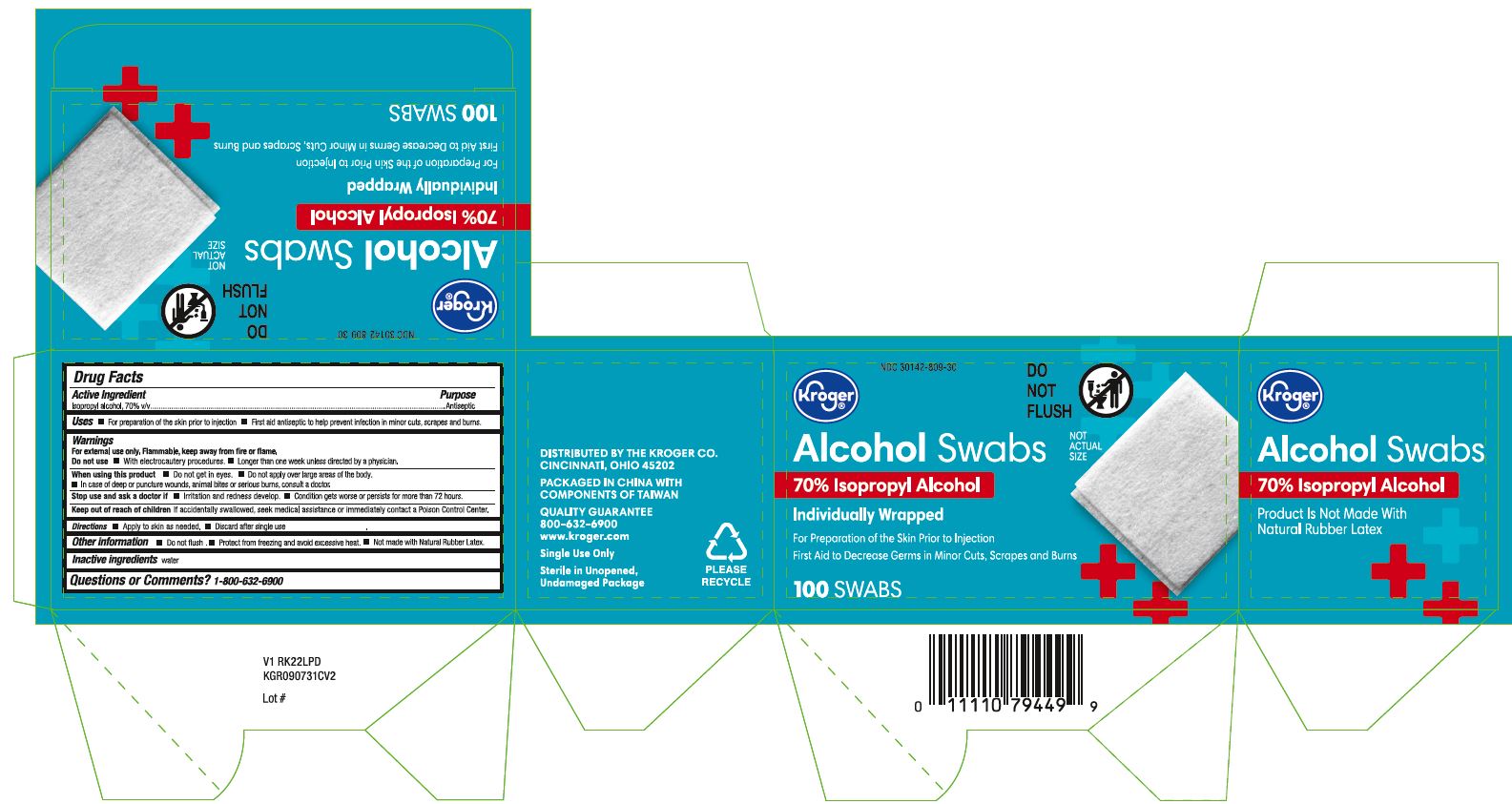 DRUG LABEL: Alcohol
NDC: 30142-809 | Form: SWAB
Manufacturer: The Kroger Company
Category: otc | Type: HUMAN OTC DRUG LABEL
Date: 20250103

ACTIVE INGREDIENTS: ISOPROPYL ALCOHOL 70 mL/100 mL
INACTIVE INGREDIENTS: WATER

30142-809 Kroger Alcohol Prep Pads

Active ingredient

Isopropyl alcohol 70% v/v

Purpose

First aid antiseptic

Uses

- first aid to help prevent infection in minor cuts, scrapes and burns

Warnings

- For external use only.
- Flammable. Keep away from fire or flame.

Do not use

- • with electrocautery procedures
- • longer than 1 week unless directed by a doctor

When using this product

- • do not get into eyes
- • do not apply over large areas of the body
- • in case of deep or puncture wounds, animal bites or serious burns, consult a doctor

Stop use and ask a doctor if

- • irritation and redness develop
- • condition gets worse or persists for more than 72 hours

Keep out of reach of children.

If accidentally swallowed, get medical help or contact a Poison Control Center right away.

Directions

- • apply to skin as needed
- • discard after single use

Other information

- do not flush
- protect from freezing and avoid excessive heat
- not made with natural rubber latex

Inactive Ingredients

water

Manufacturing Information

Distributed by:

The Kroger Co.

1014 Vine Street, Cincinnati, OH 45202

Packaged in China with components of Taiwan

800-632-6900

www.kroger.com

REF: KGR090731CV2

V1 RK22LPD